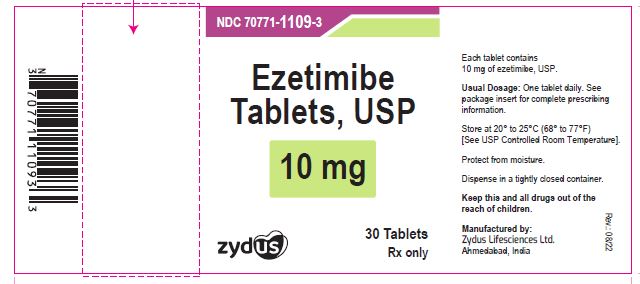 DRUG LABEL: ezetimibe
NDC: 70771-1109 | Form: TABLET
Manufacturer: Zydus Lifesciences Limited
Category: prescription | Type: HUMAN PRESCRIPTION DRUG LABEL
Date: 20241128

ACTIVE INGREDIENTS: EZETIMIBE 10 mg/1 1
INACTIVE INGREDIENTS: CELLULOSE, MICROCRYSTALLINE; CROSPOVIDONE; LACTOSE MONOHYDRATE; MAGNESIUM STEARATE; POVIDONE; SODIUM LAURYL SULFATE; SODIUM STEARYL FUMARATE; STARCH, CORN

EZETIMIBE TABLETS

PACKAGE LABEL

NDC 70771-1109-3 in bottle of 30 tablets

Ezetimibe Tablets , 10 mg

Rx only

30 tablets